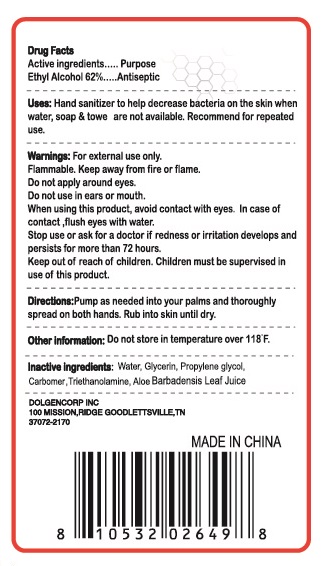 DRUG LABEL: anti bacterial hand sanitizer
NDC: 55910-988 | Form: GEL
Manufacturer: Dolgencorp Inc.
Category: otc | Type: HUMAN OTC DRUG LABEL
Date: 20160221

ACTIVE INGREDIENTS: ALCOHOL 62 mL/100 mL
INACTIVE INGREDIENTS: WATER; ALOE VERA LEAF; GLYCERIN; PROPYLENE GLYCOL; CARBOMER INTERPOLYMER TYPE A (55000 CPS); TROLAMINE

Active Ingredients:
Ethyl Alcohol 62%

Purpose:
Antiseptic

Warnings: For external use only.

Flammable. Keep away from fire or flame.

Do not apply around eyes.

Do not use in ears or mouth.

When using this product, avoid contact with eyes. In case of contact, flush eyes with water.

Stop use or ask for a doctor if redness or irritation develops and persists for more than 72 hours.

Keep out of reach of children. Children must be supervised in use of this product.

Directions:
Pump as needed into your palms and thoroughly spread on both hands. Rub into skin until dry.

INACTIVE INGREDIENT

Inactive ingredients: Water, Glycerin, Propylene Glycol, Carbomer, Triethanolamine, Aloe Barbadenis Leaf Juice

Other information: Do not store in temperature over 118 F.

INDICATIONS AND USAGE

Uses: Hand sanitizer to help decrease bacteria on the skin when water, soap & towel are not available. Recommended for repeated use.